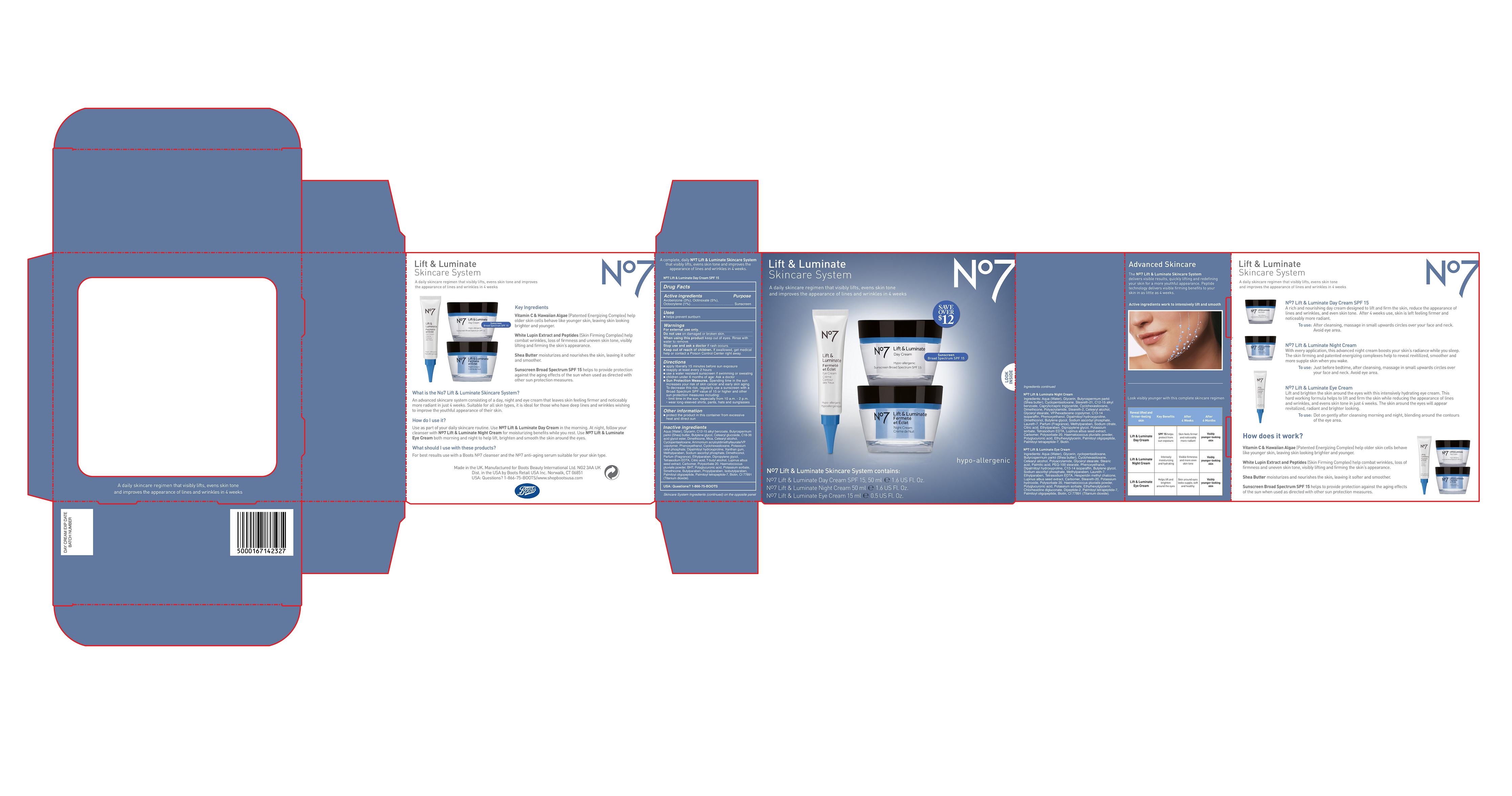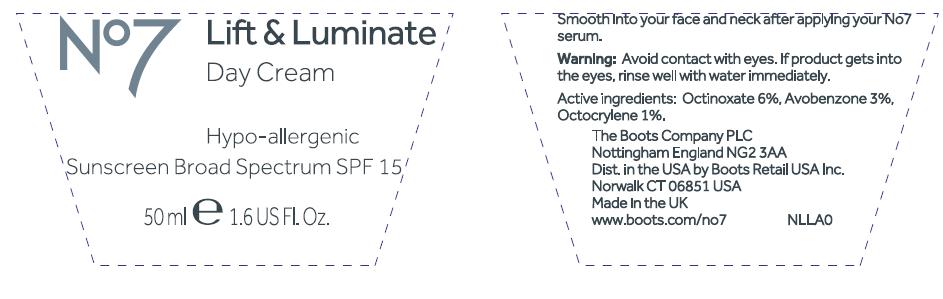 DRUG LABEL: No7 Lift and Luminate Day Sunscreen Broad Spectrum SPF 15
NDC: 68472-114 | Form: EMULSION
Manufacturer: Boots Retail USA Inc
Category: otc | Type: HUMAN OTC DRUG LABEL
Date: 20120530

ACTIVE INGREDIENTS: Avobenzone 1.5 mL/50 mL; Octinoxate 2.5 mL/50 mL; Octocrylene 0.5 mL/50 mL
INACTIVE INGREDIENTS: Water; Glycerin; ALKYL (C12-15) BENZOATE; SHEA BUTTER; BUTYLENE GLYCOL; CETEARYL GLUCOSIDE; Dimethicone; mica; CETOSTEARYL ALCOHOL; CYCLOMETHICONE 5; AMMONIUM ACRYLOYLDIMETHYLTAURATE/VP COPOLYMER; Phenoxyethanol; CYCLOMETHICONE 6; POTASSIUM CETYL PHOSPHATE; DIPALMITOYL HYDROXYPROLINE; XANTHAN GUM; METHYLPARABEN; SODIUM ASCORBYL PHOSPHATE; ETHYLPARABEN; DIPROPYLENE GLYCOL; EDETATE SODIUM; CITRIC ACID MONOHYDRATE; TERT-BUTYL ALCOHOL; LUPINUS ALBUS SEED; POLYSORBATE 20; HAEMATOCOCCUS PLUVIALIS; BUTYLATED HYDROXYTOLUENE; POTASSIUM SORBATE; BUTYLPARABEN; PROPYLPARABEN; ISOBUTYLPARABEN; PALMITOYL OLIGOPEPTIDE; PALMITOYL TETRAPEPTIDE-7; biotin; TITANIUM DIOXIDE

Carton and jar labelling

ACTIVE INGREDIENT

No7 Lift and Luminate Day Cream SPF 15

Drug Facts

Active Ingredients Avobenzone 3%, Octinoxate 5%, Octocrylene 1%

Purpose Sunscreen

PURPOSE

Uses helps prevent sunburn

Warnings

For external use only

Do not use on damaged or broken skin

When using this product keep out if eyes. Rinse with water to remove.

Stop use and ask a doctor if rash occurs.

Keep out of reach of children. If swallowed get medical help or contact a poison control center right away.

INDICATIONS AND USAGE

Directons

Apply liberally 15 minutes before sun exposure

Use a water resistant sunscreen if swimming or sweating

Reapply at least every 2 hours

Chidren under 6 months of age: Ask a doctor

Sun Protection Measures

Spending time in the sun increases your risk of skin cancer and early skin aging. To decrease this risk, regularly use a sunscreen with a broad spectrum SPF value of 15 or higher and other sun protection measures including:

limit time in the sun, especially from 10a,m - 2p.m

wear long-sleeved shirts, pants, hat and sunglasses

Other information

Protect the product in this container from excessive heat and direct sun

Inactive Ingredients

Aqua (water), Glycerin, C12-15 alkyl benzoate, Butyrospermum parkii (shea) butter, Butylene glycol, Cetearyl glucoside, C18-36 acid glycol ester, Dimethicone, Mica, Cetearyl alcohol, Cyclopentasiloxane, Ammonium acryloyldimethyltaurate/VP coplymer, Phenoxyethanol, Cyclohexasiloxane, Potassium cetyl phosphate, Dipalmitoyl hydroxyproline, Xanthan gum, Methylparaben, Sodium ascorbyl phosphate, Dimethiconol, Parfum (Fragrance), Ethylparaben, Dipropylene glycol, Tetrasodium EDTA, Citric acid, T-butyl alcohol, Lupinus albus seed extract, Carbomer, Polysorbate 20, Haematococcus Pluvialis powder, BHT, Polyglucuronic acid, Potassium sorbate, Simethicone, Butylparaben, Propylparaben, Isobutylparaben, Palmitoyl oligopeptide, Palmitoyl tetrapeptide-7, Biotin, CI 77891 (Titanium dioxide)

USA: Questions? 1-866-75-BOOTS

DESCRIPTION

A complete, daily no7 lift and luminate skincare system that visibly lifts, evens skin tone and improves the appearance of lines and wrinkles in 4 weeks.

INACTIVE INGREDIENT

Ingredients continued
No7 lift and luminate night cream
Ingredients: Aqua (water), glycerin, butyrospermum parkii (shea butter), cyclopentasiloxane, steareth-21, c12-15 alkyl benzoate, caprylic/capric triglyceride, cyclohexasiloxane, dimethicone, polyacrylamide, steareth-2, cetearyl alcohol, glyceryl stearate, vp/hexadecene copolymer, c13-14 isoparaffin, phenoxyethanol, dipalmitoyl hydroxyproline, dimethiconol, butylene glycol, sodium ascorbyl phosphate, laureth-7, parfum (fragrance), methylparaben, sodium citrate, citric acid, ethylparaben, dipropylene glycol, potassium sorbate, tetrasodium EDTA, lupinus albus seed extract, carbomer, polysorbate 20, haematococcus pluvialis powder, polyglucuronic acid, ethylhexylglycerin, palmitoyl oligopeptide, palmitoyl tetrapeptide-7, biotin.
No7 lift and luminate eye cream
Ingredients: Aqua (water), glycerin, cyclopentasiloxane, butyrospermum parkii (shea butter), cyclohexasiloxane, cetearyl alcohol, polyacrylamide, glyceryl stearate, stearic acid, palmitic acid, PEG-100 stearate, phenoxyethanol, dipalmitoyl hydroxyproline, C13-14 isoparaffin, butylene glycol, sodium ascorbyl phosphate, methylparaben, laureth-7, ethylparaben, tetrasodium EDTA, hesperidn methyl chalcone, lupinus albus seed extract, carbomer, steareth-20, potassium hydroxide, polysorbate 20, haematococcus pluvialis powder, polyglucuronic acid, potassium sorbate, ethylhexylglycerin, chlorhexidine digluconate, dipeptide-2, palmitoyl tetrapeptide-7, palmitoyl oligopeptide, biotin, CI 77891 (titanium dioxide).

DESCRIPTION

Lift and luminate No7
Skincare system
A daily skincare regimen that visibly lifts, evens skin tone and improves the appearance of lines and wrinkles in 4 weeks.
Key ingredients
Vitamin C and Hawaiian algae (Patented energizing complex) help older skin cells behave like younger skin, leaving skin looking brighter and younger.
White lupin extract and peptides (Skin firming complex) help combat wrinkles, loss of firmness and uneven skin tone, visibly lifting and firming the skin's appearance.
Shea butter moisturizes and nourishes the skin, leaving it softer and smoother.
Sunscreen broad spectrum SPF 15 helps to provide protection against the aging effects of the sun when used as directed with other sin protecting measures.
What is the No7 lift and luminate skincare system?
An advanced skincare system consisting of a day, night and eye cream that leaves skin feeling firmer and noticeably more radiant in just 4 weeks. Suitable for all skin types, it is ideal for those who have deep lines and wrinkles wishing to improve the youthful appearance of their skin.
How do I use it?
Use as part of your daily skincare routine. Use No7 lift and luminate day cream in the morning. At night, follow your cleanser with No7 lift and luminate night cream for moisturizing benefits while you rest. Use No7 lift and luminate eye cream both morning and night to help lift, brighten and smooth the skin around the eyes.
What should I use with these products?
For best results use with Boots No7 cleanser and the No7 anti-aging serum suitable for your skin type.

DESCRIPTION

Advanced Skincare
The No7 lift and luminate skincare system delivers visible results, quickly lifting and redefining your skin for a more youthful appearance. Peptide technology delivers visible firming benefits to your skin in as little as 4 weeks.
Active ingredients work to intensively lift and smooth
Look visibly younger with this complete skincare regimen.

Reveal lifted and firmer-feeling skin | Key Benefits | After 4 weeks | After 6 months
Lift and luminate day cream | SPF 15 helps protect from sun exposure | Skin feels firmer and noticeably more radiant | Visibly younger-looking skin
Lift and luminate night cream | Intensely moisturizing and hydrating | Visible firmness and more even skin tone | Visibly younger-looking skin
Lift and luminate eye cream | Helps lift and brighten around the eyes | Skin around eyes looks supple, soft and healthy | Visibly younger-looking skin

INSTRUCTIONS FOR USE

Lift and luminate No7
Skincare system
A daily skincare regimen that visibly lifts, evens the skin tone and improves the appearance of lines and wrinkles in 4 weeks.
No7 lift and luminate day cream SPF 15
A rich and nourishing day cream designed to lift and firm the skin, reduce the appearance of lines and wrinkles, and even skin tone. After 4 weeks use, skin is left feeling firmer and noticeably more radiant.
To use: After cleansing, massage in small upwards circles over your face and neck. Avoid eye area.
No7 lift and luminate night cream
With every application, this advanced night cream boosts your skin's radiance while you sleep. The skin firming and patented energizing complexes help to reveal revitalized, smoother and more supple skin when you wake.
To use: Just before bedtime, after cleansing, massage in small upwards circles over your face and neck. Avoid eye area.
No7 lift and luminate eye cream
Lift and brighten the skin around the eyes with this intensively hydrating eye cream. This hard working formula helps to lift and firm the skin while reducing the appearance of lines and wrinkles, and evens skin tone in just 4 weeks. The skin around the eyes will appear revitalised, radiant and brighter looking.
To use: Dot on gently after cleansing morning and night, blending around the contours of the eye area.
How does it work?
Vitamin C and Hawaiian algae (Patented energizing complex) help older skin cells behave like younger skin, leaving skin looking brighter and younger.
White lupin extract and peptides (Skin firming complex) help combat wrinkles, loss of firmness and uneven skin tone, visibly lifting and firming the skin's appearance.
Shea butter moisturizes and nourishes the skin, leaving it softer and smoother.
Sunscreen broad spectrum SPF 15 helps to provide protection against the aging effects of the sun when used as directed with other sin protecting measures.

PATIENT COUNSELING INFORMATION

Made in the UK. Manufactured for Boots Beauty International Ltd. NG2 3AA UK.
Dist. in the USA by Boots Retail USA Inc. Norwalk, CT 06851
USA: Questions? 1-866-75-BOOTS www.shopbootsusa.com

ACTIVE INGREDIENT

JAR TEXT

Active ingredients: Octinoxate 6%, Avobenzone 3%, Octocrylene 1%

WARNINGS AND PRECAUTIONS

JAR TEXT

Warning: Avoid contact with eyes. If product gets into the eyes rinse well with water immediately.

INDICATIONS AND USAGE

JAR TEXT

Smooth into your face and neck after applying your No7 serum.

PATIENT COUNSELING INFORMATION

JAR TEXT
The Boots Company PLC Nottingham England NG2 3AA
Dist. in the USA by Boots Retail USA Inc. Norwalk CT 06851 USA
Made in the UK
www.Boots.com no7

PACKAGE LABEL

No7 Lift and Luminate
Skincare system
A daily skincare regimen that visibly lifts, evens skin tone and improves the appearance of lines and wrinkles in 4 weeks.
Save over 12 dollars
Sunscreen broad spectrum
Look inside
Hypoallergenic
No7 lift and luminate skincare system contains:
No7 lift and luminate day cream SPF 15 50 ml 1.6 US Fl. Oz
No7 lift and luminate night cream 50 ml 1.6 US Fl. Oz
No7 lift and luminate eye cream 15 ml 0.5 US Fl. Oz

No7 LL Day Cream Kit carton.jpg

PACKAGE LABEL

JAR TEXT
No7 Protect and Perfect Day Cream
Hypo-allergenic
Sunscreen Broad Spectrum SPF 15
50ml 1.6 US Fl.Oz
No7 LL Day Cream SPF 15 jar.jpg